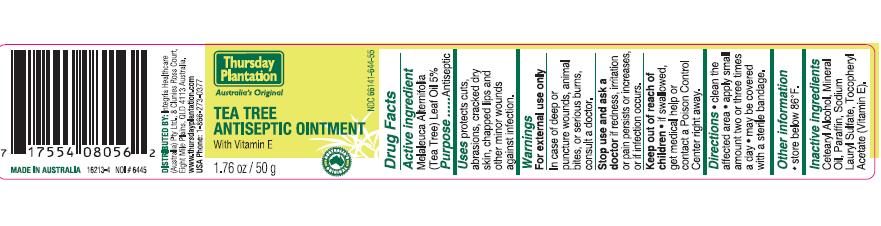 DRUG LABEL: Thursday Plantation
NDC: 66141-644 | Form: OINTMENT
Manufacturer: Integria Healthcare Ballina
Category: otc | Type: HUMAN OTC DRUG LABEL
Date: 20100218

ACTIVE INGREDIENTS: TEA TREE OIL 3 g/50 g

ACTIVE INGREDIENT

Melaleuca Alternifolia (Tea Tree) Leaf Oil 5% ...... Antiseptic

INDICATIONS AND USAGE

Uses: protects cuts, abrasions, cracked dry skin, chapped lips and other minor wounds against infection.

WARNINGS

For external use only.

In case of deep or puncture wounds, animal bites, or serious burns, consult a doctor.

Stop use and ask a doctor if redness, irritation or pain persists or increases, or if infection occurs.

Keep out of reach of children. If swallowed, get medical help or contact a Poison Control Center right away.

PURPOSE

Antiseptic

DOSAGE AND ADMINISTRATION

Directions: clean the affected area. apply small amount two or three times a day. may be covered with a sterile bandage.

STORAGE AND HANDLING

store below 86 degrees F.

PACKAGE LABEL

Thursday Plantation

Australia's Original

Tea Tree Antiseptic

With Vitamin E

Distributed By:
Integria Healthcare Australia
Pty Ltd 8 Clunies Ross Court
Eight Mile Plains, QLD 4113
Australia
www.thursdayplantation.com
USA Phone: 1-866-273-0377
Made in Australia

INACTIVE INGREDIENT

Inactive Ingredients: Cetearyl Alcohol, Mineral Oil, Paraffin, Sodium Lauryl Sulfate, Tocopheryl Acetate (vitamin E).